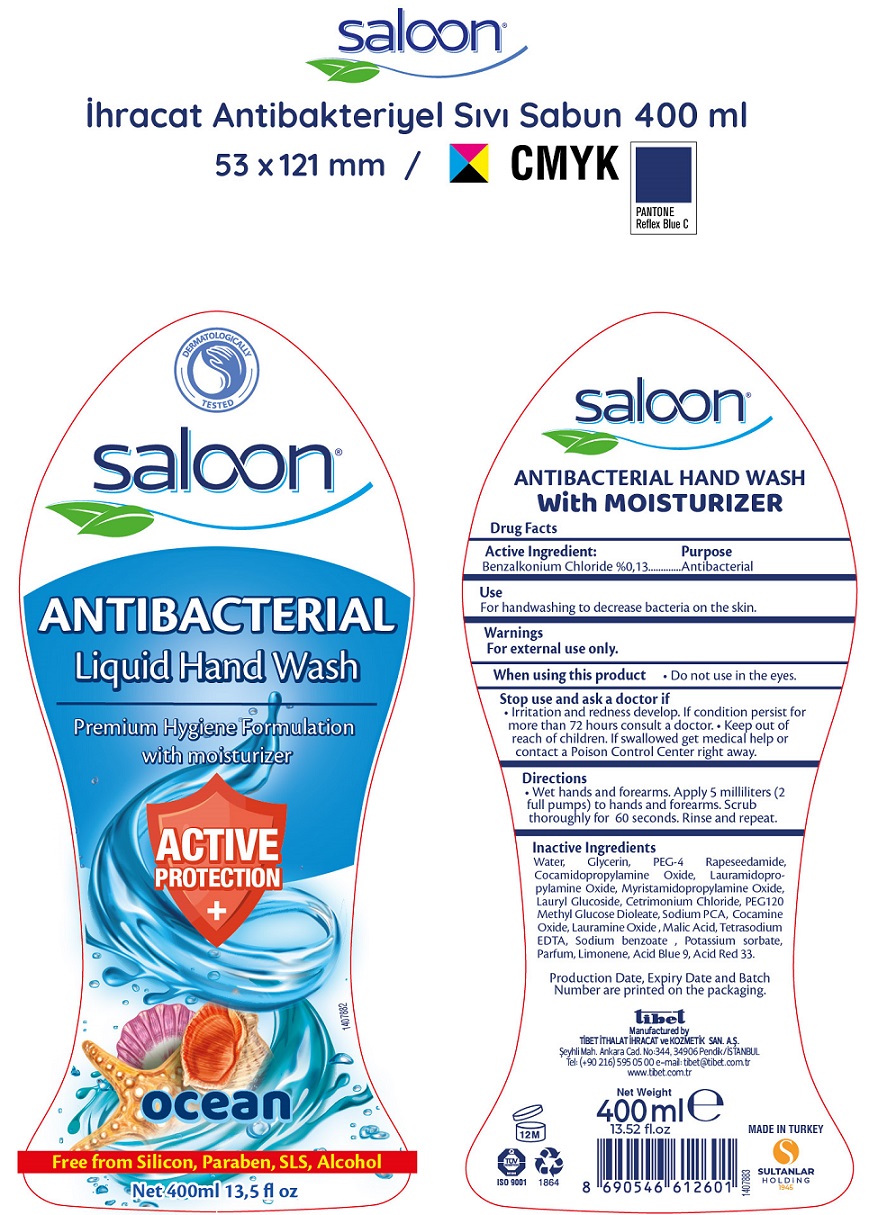 DRUG LABEL: Saloon Antibacterial Hand Wash Ocean
NDC: 81608-003 | Form: SOLUTION
Manufacturer: TIBET ITHALAT IHRACAT VE KOZMETIK SANAYI ANONIM SIRKETI
Category: otc | Type: HUMAN OTC DRUG LABEL
Date: 20210421

ACTIVE INGREDIENTS: BENZALKONIUM CHLORIDE 1.3 mg/1 mL
INACTIVE INGREDIENTS: WATER; GLYCERIN; PEG-4 RAPESEEDAMIDE; COCAMIDOPROPYLAMINE OXIDE; LAURAMIDOPROPYLAMINE OXIDE; MYRISTAMIDOPROPYLAMINE OXIDE; LAURYL GLUCOSIDE; CETRIMONIUM CHLORIDE; PEG-120 METHYL GLUCOSE DIOLEATE; SODIUM PYRROLIDONE CARBOXYLATE; COCAMINE OXIDE; LAURAMINE OXIDE; MALIC ACID; EDETATE SODIUM; SODIUM BENZOATE; POTASSIUM SORBATE; FD&C BLUE NO. 1; D&C RED NO. 33; LIMONENE, (+)-

Saloon Antibacterial Hand Wash Ocean

Active Ingredient:

Benzalkonium chloride %0,13

Purpose

Antibacterial

Use

For handwashing to decrease bacteria on the skin.

Warnings

For external use only.

When using this product

- Do not use in the eyes.

Stop use and ask a doctor if

- Irritation and redness develop. If condition persist for more than 72 hours consult a doctor.

Keep out of reach of children.

If swallowed, get medical help or contact a Poison Control Center right away.

Directions

- Wet hands and forearms. Apply 5 milliliters (2 full pumps) to hands and forearms. Scrub thoroughly for 60 seconds. Rinse and repeat.

Inactive Ingredients

Water, Glycerin, PEG-4 Rapeseedamide, Cocamidopropylamine Oxide, Lauramidopropylamine Oxide, Myristamidopropylamine Oxide, Lauryl Glucoside, Cetrimonium Chloride, PEG 120 Methyl Glucose Dioleate, Sodium PCA, Cocamine Oxide, Lauramine Oxide, Malic Acid, Tetrasodium EDTA, Sodium Benzoate, Potassium sorbate, Parfum, Acid Blue 9, Acid Red 33.